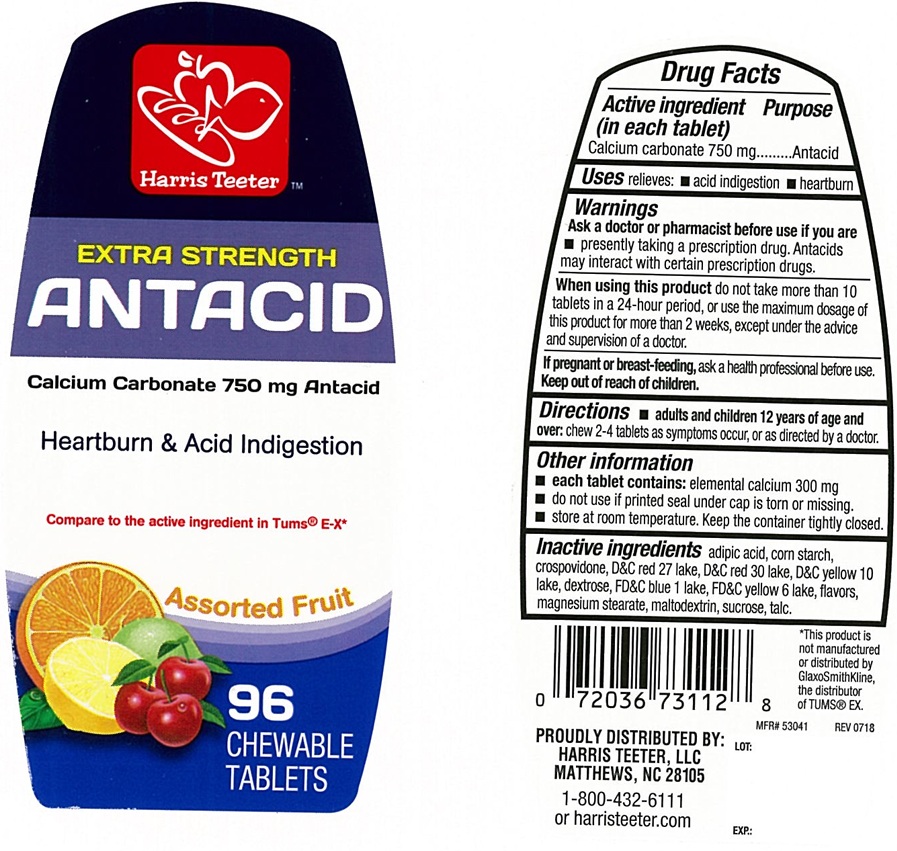 DRUG LABEL: Extra Strength Assorted Fruit Antacid
NDC: 69256-127 | Form: TABLET, CHEWABLE
Manufacturer: Harris Teeter, LLC
Category: otc | Type: Human OTC Drug Label
Date: 20250314

ACTIVE INGREDIENTS: CALCIUM CARBONATE 750 mg/1 1
INACTIVE INGREDIENTS: ADIPIC ACID; STARCH, CORN; CROSPOVIDONE; DEXTROSE, UNSPECIFIED FORM; FD&C BLUE NO. 1 ALUMINUM LAKE; MAGNESIUM STEARATE; MALTODEXTRIN; SUCROSE; TALC; D&C RED NO. 27 ALUMINUM LAKE; D&C RED NO. 30 ALUMINUM LAKE; D&C YELLOW NO. 10 ALUMINUM LAKE; FD&C YELLOW NO. 6 ALUMINUM LAKE

Extra Strength Antacid Assorted Fruit Chewable Tablets

ACTIVE INGREDIENT (in each tablet)

Calcium carbonate 750 mg

PURPOSE

Antacid

USE(S)

relieves:

- acid indigestion
- heartburn

WARNINGS

.

ASK A DOCTOR OR PHARMACIST BEFORE USE IF YOU ARE

- presently taking a prescription drug. Antacids may interact with certain prescription drugs.

WHEN USING THIS PRODUCT

do not take more than 10 tablets in a 24-hour period, or use the maximum dosage of this product for more than 2 weeks, except under the advice and supervision of a doctor.

IF PREGNANT OR/BREASTFEEDING,

ask a health professional before use.

KEEP OUT OF REACH OF CHILDREN

.

DIRECTIONS

- adults and children 12 years of age and over: chew 2-4 tablets as symptoms occur, or as directed by a doctor.

OTHER INFORMATION

- each tablet contains: elemental calcium 300 mg
- do not use if printed seal under cap is torn or missing.
- store at room temperature.Keep the container tightly closed.

INACTIVE INGREDIENTS

adipic acid, corn starch, crospovidone, D&C red 27 lake, D&C red 30 lake, D&C yellow 10 lake, dextrose, FD&C blue 1 lake, FD&C yellow 6 lake, flavors, magnesium stearate, maltodextrin, sucrose, talc.

PRINCIPAL DISPLAY PANEL

Harris Teeter™
NDC 69256-127-22

EXTRA STRENGTH

ANTACID

Heartburn & Acid Indigestion
Compare to the active ingredient in Tums® E-X*

Assorted Fruit

96 CHEWABLE TABLETS